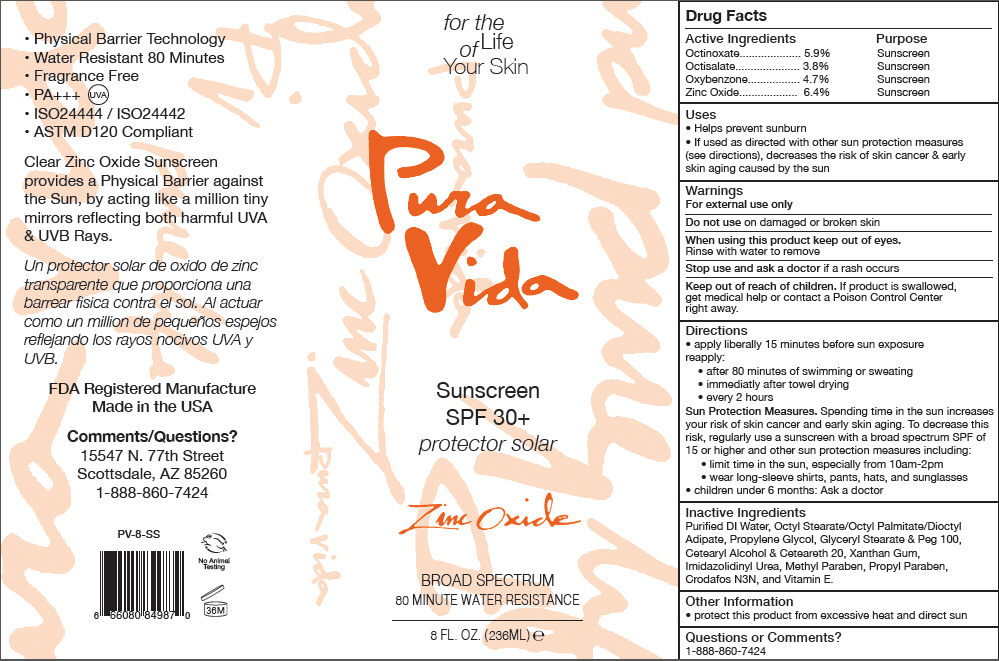 DRUG LABEL: Pura Vida Sunscreen
NDC: 59555-106 | Form: LOTION
Manufacturer: R & R Lotion, Inc
Category: otc | Type: HUMAN OTC DRUG LABEL
Date: 20210115

ACTIVE INGREDIENTS: Zinc Oxide 64 mg/1 mL; Octinoxate 59 mg/1 mL; Octisalate 38 mg/1 mL; Oxybenzone 47 mg/1 mL
INACTIVE INGREDIENTS: Water; Xanthan Gum; Propylene Glycol; Methylparaben; Diethylhexyl Adipate; Ethylhexyl Palmitate; Ethylhexyl Stearate; Cetostearyl Alcohol; Polyoxyl 20 Cetostearyl Ether; .Alpha.-Tocopherol; Imidurea; Diethanolamine Oleth-3 Phosphate; Glyceryl Monostearate; Peg-100 Stearate; Propylparaben

Pura Vida Sunscreen

Drug Facts

ACTIVE INGREDIENT

Active Ingredients | Purpose
Octinoxate 5.9% | Sunscreen
Octisalate 3.8% | Sunscreen
Oxybenzone 4.7% | Sunscreen
Zinc Oxide 6.4% | Sunscreen

Uses

- Helps prevent sunburn
- If used as directed with other sun protection measures (see directions), decreases the risk of skin cancer & early skin aging caused by the sun

Warnings

For external use only

Do not use on damaged or broken skin

When using this product keep out of eyes.

Rinse with water to remove

Stop use and ask a doctor if a rash occurs

Keep out of reach of children. If product is swallowed, get medical help or contact a Poison Control Center right away.

Directions

- apply liberally 15 minutes before sun exposure reapply:
  - after 80 minutes of swimming or sweating
  - immediatly after towel drying
  - every 2 hours

Sun Protection Measures. Spending time in the sun increases your risk of skin cancer and early skin aging. To decrease this risk, regularly use a sunscreen with a broad spectrum SPF of 15 or higher and other sun protection measures including:

  - limit time in the sun, especially from 10am-2pm
  - wear long-sleeve shirts, pants, hats, and sunglasses

- children under 6 months: Ask a doctor

Inactive Ingredients

Purified DI Water, Octyl Stearate/Octyl Palmitate/Dioctyl Adipate, Propylene Glycol, Glyceryl Stearate & Peg 100, Cetearyl Alcohol & Ceteareth 20, Xanthan Gum, Imidazolidinyl Urea, Methyl Paraben, Propyl Paraben, Crodafos N3N, and Vitamin E.

Other Information

- protect this product from excessive heat and direct sun

Questions or Comments?

1-888-860-7424

PRINCIPAL DISPLAY PANEL - 236 ML Bottle Label

for the
Life
of
Your Skin

Pura
Vida

Sunscreen
SPF 30+
protector solar

Zinc Oxide

BROAD SPECTRUM
80 MINUTE WATER RESISTANCE

8 FL. OZ. (236ML) e